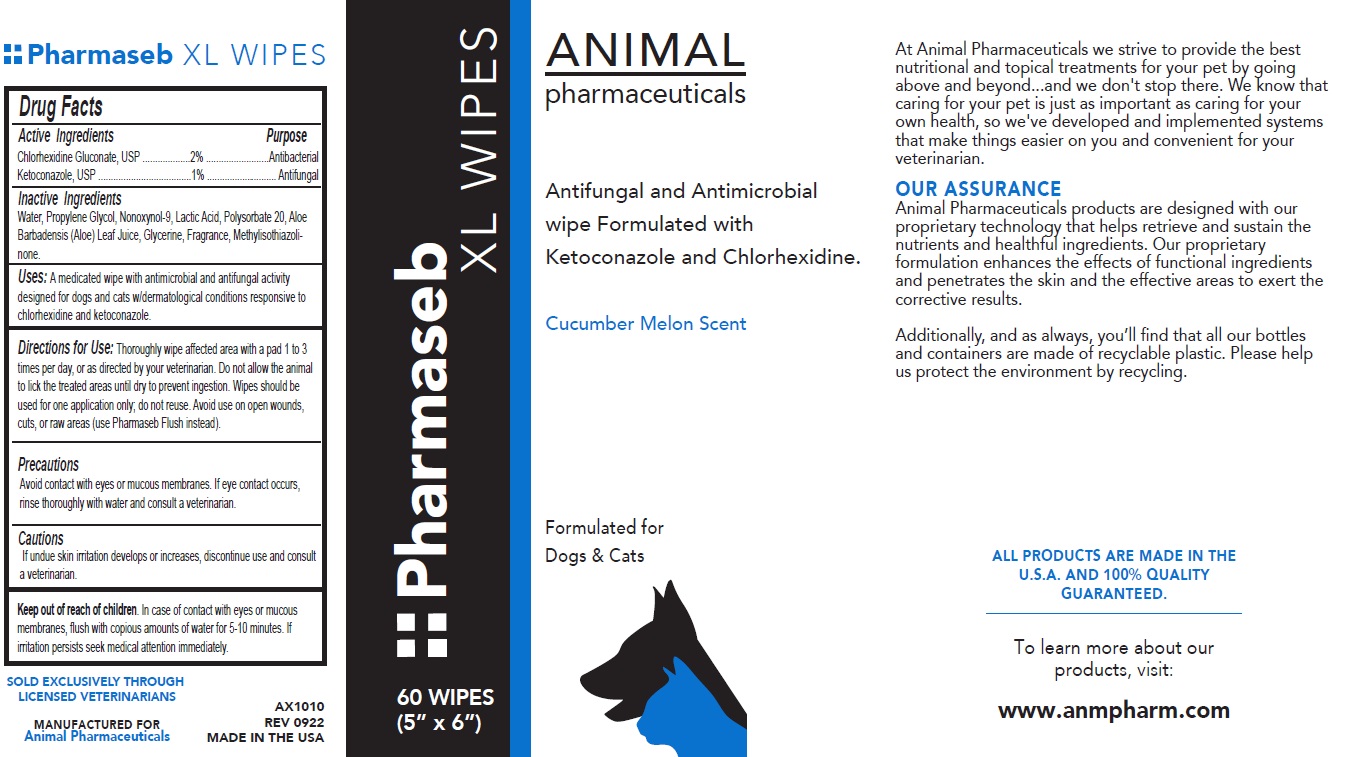 DRUG LABEL: Pharmaseb XL WIPES 60 count
NDC: 68898-130 | Form: CLOTH
Manufacturer: Animal Pharmaceuticals
Category: animal | Type: OTC ANIMAL DRUG LABEL
Date: 20230623

ACTIVE INGREDIENTS: CHLORHEXIDINE GLUCONATE 2 g/100 mL; KETOCONAZOLE 1 g/100 mL
INACTIVE INGREDIENTS: WATER; PROPYLENE GLYCOL; NONOXYNOL-9; LACTIC ACID, UNSPECIFIED FORM; POLYSORBATE 20; ALOE VERA LEAF; GLYCERIN; METHYLISOTHIAZOLINONE

Pharmaseb XL WIPES

Active Ingredients

Chlorhexidine Gluconate, USP ..............2%
Ketoconazole, USP ..............................1%

Purpose

Antibacterial
Antifungal

Inactive Ingredients

Water, Propylene Glycol, Nonoxynol-9, Lactic Acid, Polysorbate 20, Aloe Barbadensis (Aloe) Leaf Juice, Glycerine, Fragrance, Methylisothiazolinone.

Uses:

A medicated wipe with antimicrobial and antifungal activity designed for dogs and cats w/dermatological conditions responsive to chlorhexidine and ketoconazole.

Directions for Use:

Thoroughly wipe affected area with a pad 1 to 3 times per day, or as directed by your veterinarian. Do not allow the animal to lick the treated areas until dry to prevent ingestion. Wipes should be used for one application only; do not reuse. Avoid use on open wounds, cuts, or raw areas (use Pharmaseb Flush instead).

Precautions

Avoid contact with eyes or mucous membranes. If eye contact occurs, rinse thoroughly with water and consult a veterinarian.

Cautions

If undue skin irritation develops or increases, discontinue use and consult a veterinarian.

Keep out of reach of children. In case of contact with eyes or mucous membranes, flush with copious amounts of water for 5-10 minutes. If irritation persists seek medical attention immediately.

Antifungal and Antimicrobial wipe Formulated with Ketoconazole and Chlorhexidine.

Cucumber Melon Scent

Formulated for Dogs & Cats

At Animal Pharmaceuticals we strive to provide the best nutritional and topical treatments for your pet by going above and beyond...and we don't stop there. We know that caring for your pet is just as important as caring for your own health, so we've developed and implemented systems that make things easier on you and convenient for your veterinarian.

OUR ASSURANCE
Animal Pharmaceuticals products are designed with our proprietary technology that helps retrieve and sustain the nutrients and healthful ingredients. Our proprietary formulation enhances the effects of functional ingredients and penetrates the skin and the effective areas to exert the corrective results.

Additionally, and as always, you’ll find that all our bottles and containers are made of recyclable plastic. Please help us protect the environment by recycling.

ALL PRODUCTS ARE MADE IN THE U.S.A. AND 100% QUALITY GUARANTEED.

To learn more about our products, visit:
www.anmpharm.com

SOLD EXCLUSIVELY THROUGH LICENSED VETERINARIANS

MANUFACTURED FOR
Animal Pharmaceuticals

MADE IN THE USA